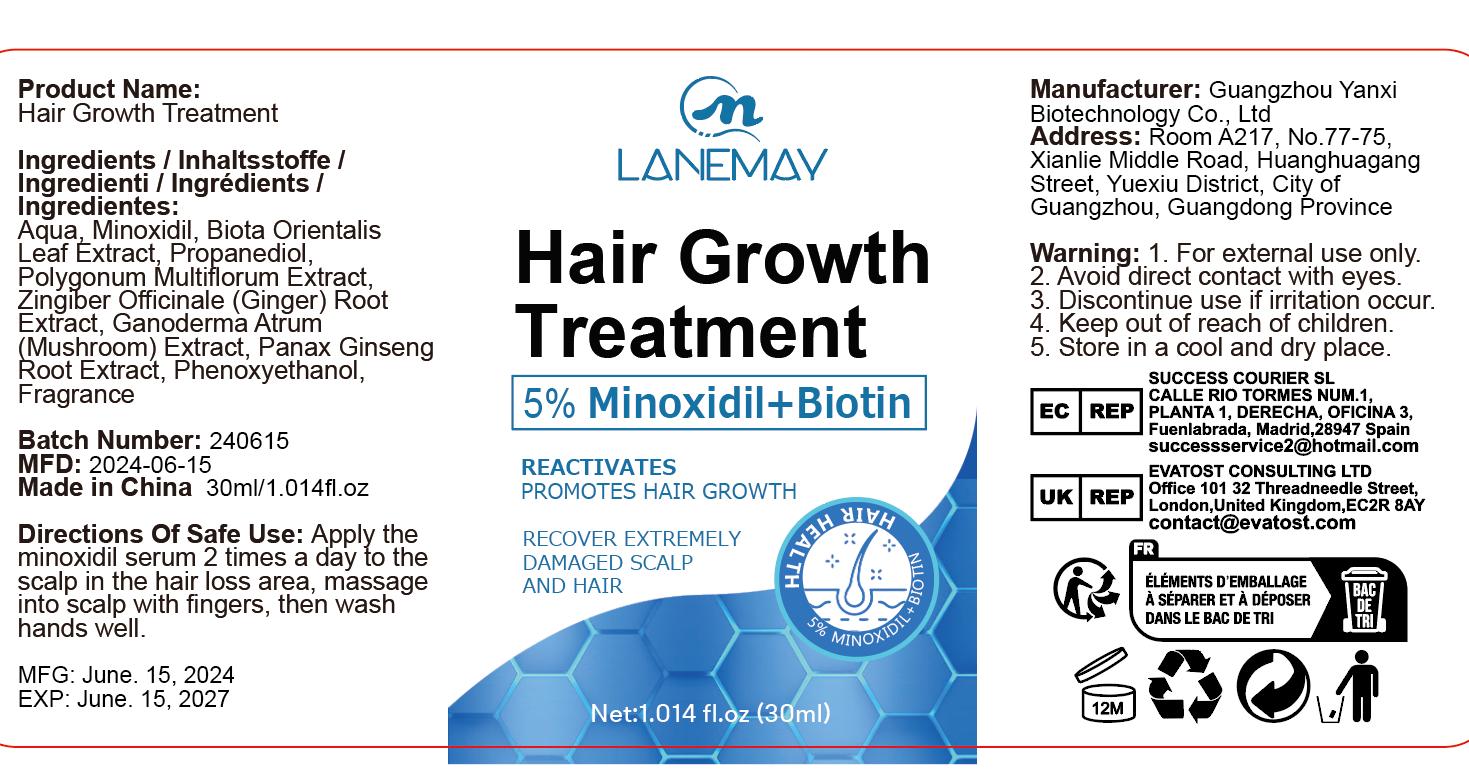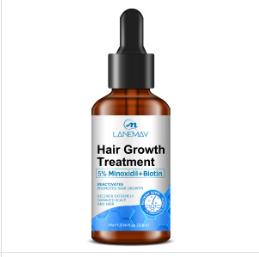 DRUG LABEL: Hair Growth Treatment
NDC: 84025-053 | Form: CREAM
Manufacturer: Guangzhou Yanxi Biotechnology Co., Ltd
Category: otc | Type: HUMAN OTC DRUG LABEL
Date: 20240709

ACTIVE INGREDIENTS: PROPANEDIOL 2 mg/30 mL; MINOXIDIL 3 mg/30 mL
INACTIVE INGREDIENTS: WATER

DOSAGE AND ADMINISTRATION

use as a normal hair cream

WARNINGS

Keep out of Children

INACTIVE INGREDIENT

Aqua

INDICATIONS AND USAGE

For daily hair care

PURPOSE

Keep out of Children

Keep out of Children